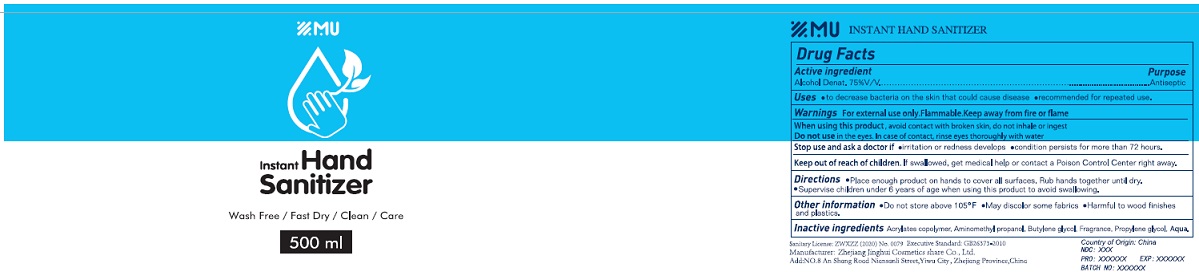 DRUG LABEL: MU instant hand sanitizer
NDC: 78422-001 | Form: GEL
Manufacturer: Ningbo Royal Union Co., Ltd.
Category: otc | Type: HUMAN OTC DRUG LABEL
Date: 20200529

ACTIVE INGREDIENTS: ALCOHOL 75 mL/100 mL
INACTIVE INGREDIENTS: WATER; POLYACRYLIC ACID (250000 MW); BUTYLENE GLYCOL; PROPYLENE GLYCOL; AMINOMETHYLPROPANOL

Active Ingredient

Alcohol Denat. 75% v/v.

Purpose

Antiseptic

Uses

- to decrease bacteria on the skin that could cause disease.
- recommended for repeated use.

Warnings

For external use only. Flammable. Keep away from fire or flame.
When using this product, avoid contact with broken skin, do not inhale or ingest.
Do not use in the eyes. In case of contact, rinse eyes thoroughly with water.
Stop use and ask a doctor if

- irritation or redness develops
- condition persists for more than 72 hours.

Keep out of reach of children. If swallowed, get medical help or contact a Poison Control Center right away.

Directions

•Place enough product on hands to cover all surfaces. Rub hands together until dry.
•Supervise children under 6 years of age when using this product to avoid swallowing.

Other information

- Do not store above 105°F.
- May discolor some fabrics.
- Harmful to wood finishes and plastics.

Inactive ingredients

Water, acrylic acid homopolymer, Butane-1,3-diol, 1,1-propanediol, monoisobutanolamine, Fragrance